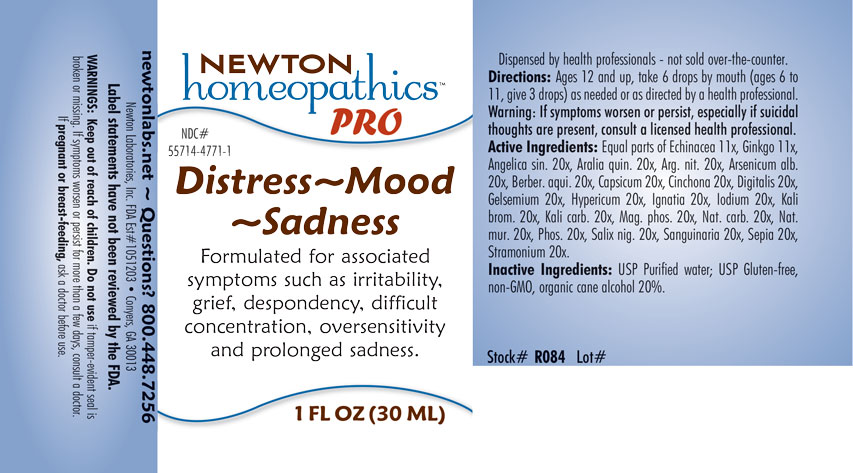 DRUG LABEL: Distress-Mood-Sadness
NDC: 55714-4771 | Form: LIQUID
Manufacturer: Newton Laboratories, Inc.
Category: homeopathic | Type: HUMAN OTC DRUG LABEL
Date: 20201202

ACTIVE INGREDIENTS: ECHINACEA, UNSPECIFIED 11 [hp_X]/1 mL; GINKGO 11 [hp_X]/1 mL; BERBERIS AQUIFOLIUM ROOT BARK 20 [hp_X]/1 mL; ANGELICA SINENSIS ROOT 20 [hp_X]/1 mL; AMERICAN GINSENG 20 [hp_X]/1 mL; SILVER NITRATE 20 [hp_X]/1 mL; ARSENIC TRIOXIDE 20 [hp_X]/1 mL; CAPSICUM 20 [hp_X]/1 mL; CINCHONA OFFICINALIS BARK 20 [hp_X]/1 mL; DIGITALIS 20 [hp_X]/1 mL; GELSEMIUM SEMPERVIRENS ROOT 20 [hp_X]/1 mL; HYPERICUM PERFORATUM 20 [hp_X]/1 mL; STRYCHNOS IGNATII SEED 20 [hp_X]/1 mL; IODINE 20 [hp_X]/1 mL; POTASSIUM BROMIDE 20 [hp_X]/1 mL; POTASSIUM CARBONATE 20 [hp_X]/1 mL; MAGNESIUM PHOSPHATE, DIBASIC TRIHYDRATE 20 [hp_X]/1 mL; SODIUM CARBONATE 20 [hp_X]/1 mL; SODIUM CHLORIDE 20 [hp_X]/1 mL; PHOSPHORUS 20 [hp_X]/1 mL; SALIX NIGRA BARK 20 [hp_X]/1 mL; SANGUINARIA CANADENSIS ROOT 20 [hp_X]/1 mL; SEPIA OFFICINALIS JUICE 20 [hp_X]/1 mL; DATURA STRAMONIUM 20 [hp_X]/1 mL
INACTIVE INGREDIENTS: WATER; ALCOHOL

Distress 4771L

INDICATIONS & USAGE SECTION

Formulated for associated symptoms such as irritability, grief, despondency, difficult concentration, oversensitivity and prolonged sadness.

DOSAGE & ADMINISTRATION SECTION

Directions: Ages 12 and up, take 6 drops by mouth (ages 6 to 11, give 3 drops) as needed or as directed by a health professional. Warning: If symptoms worsen or persist, especially if suicidal thouhts are present, consult a licensed health professional.

OTC - ACTIVE INGREDIENT SECTION

Equal parts of Echinacea 11x, Ginkgo 11x, Angelica sin. 20x, Aralia quin. 20x, Arg. nit. 20x, Arsenicum alb. 20x, Berber. aqui. 20x, Capsicum 20x, Cinchona 20x, Digitalis 20x, Gelsemium 20x, Hypericum 20x, Ignatia 20x, Iodium 20x, Kali brom. 20x, Kali carb. 20x, Mag. phos. 20x, Nat. carb. 20x, Nat. mur. 20x, Phos. 20x, Salix nigra 20x, Sanguinaria 20x, Sepia 20x, Stramonium 20x.

OTC - PURPOSE SECTION

Formulated for associated symptoms such as irritability, grief, despondency, difficult concentration, oversensitivity and prolonged sadness.

INACTIVE INGREDIENT SECTION

Inactive Ingredients: USP Purified Water; USP Gluten-free, non-GMO, organic cane alcohol 20%.

QUESTIONS SECTION

newtonlabs.net – Questions? 800.448.7256

Newton Laboratories, Inc. FDA Est # 1051203 - Conyers, GA 30013

WARNINGS SECTION

WARNINGS: Keep out of reach of children. Do not use if tamper-evident seal is missing or broken. If symptoms persist for more than a few days, consult a doctor. If pregnant or breat-feeding, ask a doctor before use.

OTC - PREGNANCY OR BREAST FEEDING SECTION

If pregnant or breast-feeding, ask a doctor before use.

OTC - KEEP OUT OF REACH OF CHILDREN SECTION

Keep out of reach of children.